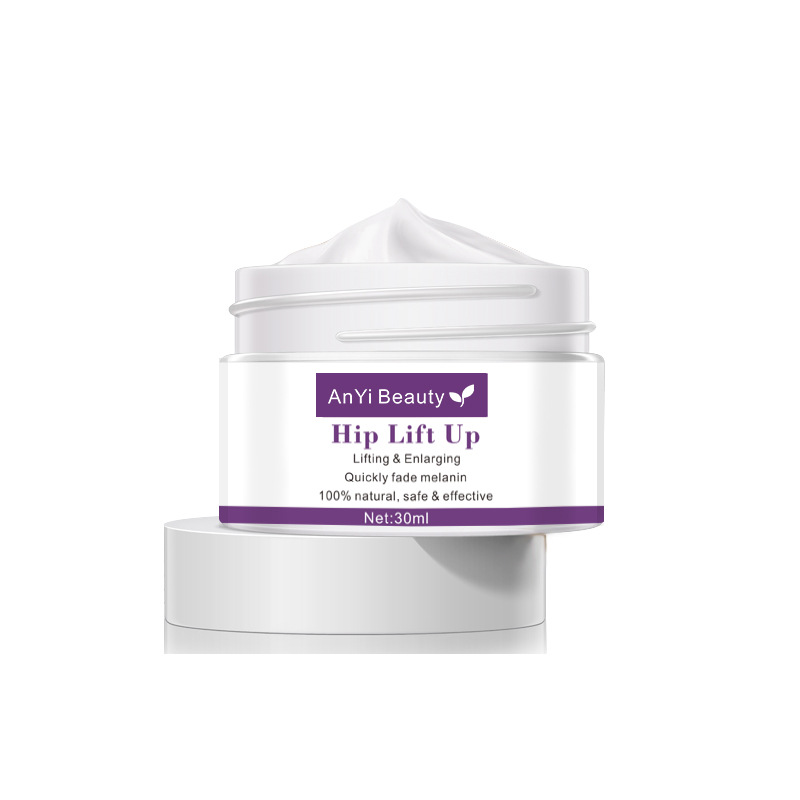 DRUG LABEL: AnYi Beauty Hip Lift Up Cream
NDC: 84037-0114 | Form: CREAM
Manufacturer: Guangzhou Zhicunxiu Cosmetics Co., Ltd
Category: otc | Type: HUMAN OTC DRUG LABEL
Date: 20241116

ACTIVE INGREDIENTS: DIMETHICONE 30 mg/1 mL
INACTIVE INGREDIENTS: PHENOXYETHANOL; CETYL ALCOHOL; METHYL GLUCOSE SESQUISTEARATE; METHYLPARABEN; C13-14 ISOPARAFFIN; WATER; MINERAL OIL; GLYCERIN; PEG-20 METHYL GLUCOSE SESQUISTEARATE

AnYi Beauty Hip Lift Up Cream

Active Ingredients

Dimethicone 3%

Purpose

Skin Protectant

Uses

- Temporarily protects and helps relieve dry or cracked skin
- Beneficlal for face, hands, body, and legs

Warnings

For external use only.

Do not useon damaged or broken skin. Do not use on individuals aged 12 and under.

When using this productavoid contact with eyes.

Please test this creamon a small patch of your the inside of the arm if it is your first time using this crea m.

Stop and ask a doctor ifirritation or allergic reactions develop.

If pregnant or breast-feeding, ask a health professional before use.

Keep out of reach of children.

In case of accidental ingestion, seek medical advice immediately orcontact a Poison Control Center right away.

Directions

After cleansing, gently massage a pea-sized amount of cream onto the skin. Use twice a day, in the morning and evening.

Other information

store in a cool dry place, away from direct sunlight.

Inactive Ingredients

Aqua, Paraffinum Liquidum, Glycerin, Cetearyl Alcohol, PEG-20 Methyl Glucose Sesquistearate,Bifida Ferment Filtrate, Methyl Glucose Sesquistearate，Methylparaben, Phenoxyethanol, C13-14 lsoparaffin, Retinyl Palmitate, Hydrogenated Jojoba Oil, Hydrogenated Olive Oil, Aloe Barbadensis Extract, Hyaluronic Acid, Hydrolyzed Collagen,Camellia Sinensis Leaf Extract, Chrysanthellum lndicum Flower Water, Tocopheryl Acetate,Fragrance,EDTA

Questions?

Email us:dengxiaobao524@gmail.com